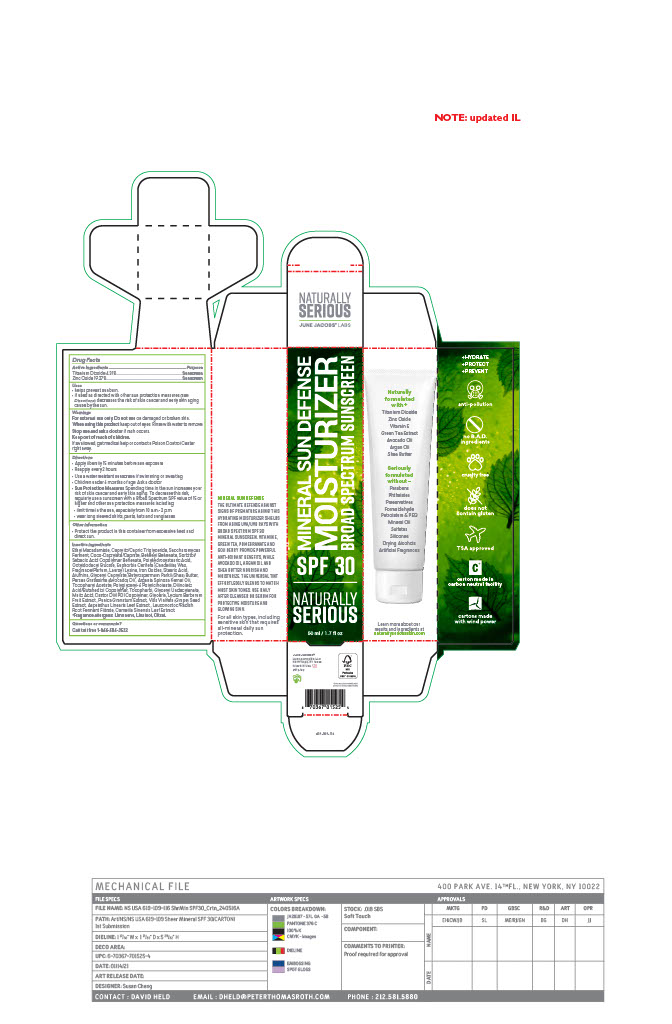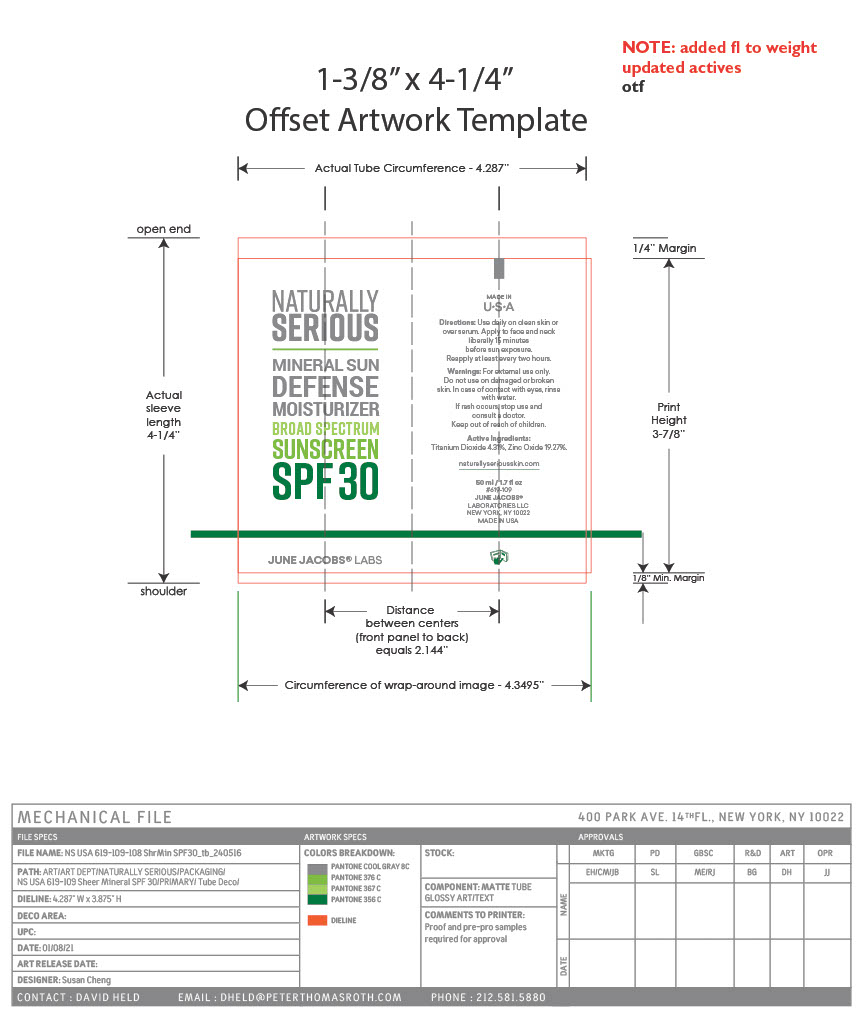 DRUG LABEL: Mineral Sun Defense Moisturizer Broad Spectrum Sunscreen SPF 30
NDC: 65278-619 | Form: PASTE
Manufacturer: June Jacobs Labs, LLC
Category: otc | Type: HUMAN OTC DRUG LABEL
Date: 20240520

ACTIVE INGREDIENTS: TITANIUM DIOXIDE 2.169 g/50.28 g; ZINC OXIDE 9.693 g/50.28 g
INACTIVE INGREDIENTS: ETHYL MACADAMIATE; ORANGE OIL; LAUROYL LYSINE; ARGAN OIL; .ALPHA.-TOCOPHEROL ACETATE; LEUCONOSTOC/RADISH ROOT FERMENT FILTRATE; COCO-CAPRYLATE/CAPRATE; GERANIUM OIL, ALGERIAN TYPE; AVOCADO OIL; TOCOPHEROL; ALUMINUM OXIDE; SACCHAROMYCES CEREVISIAE; OCTYLDODECYL ERUCATE; SUNFLOWER OIL; GLYCERYL CAPRYLATE; AMYRIS BALSAMIFERA OIL; VETIVER OIL; STEARIC ACID; SHEA BUTTER; GLYCERIN; GLYCERYL 1-UNDECYLENATE; MALIC ACID; CASTOR OIL; LINALOOL, (+/-)-; GALBANUM; DILINOLEIC ACID/BUTANEDIOL COPOLYMER; GREEN TEA LEAF; PUNICA GRANATUM ROOT BARK; CANDELILLA WAX; LAVANDIN OIL; POLYGLYCERYL-6 POLYRICINOLEATE; VITIS VINIFERA SEED; LYCIUM BARBARUM FRUIT; CITRAL; LITSEA OIL; POGOSTEMON CABLIN LEAF OIL; GINGER OIL; ASPALATHUS LINEARIS LEAF; LIMONENE, (+)-; BEHENYL BEHENATE; POLYHYDROXYSTEARIC ACID (2300 MW); JUNIPER BERRY OIL; FERRIC OXIDE RED; MEDIUM-CHAIN TRIGLYCERIDES; CAPRYLOYL GLYCERIN/SEBACIC ACID COPOLYMER (2000 MPA.S)

Sheer Mineral SPF30 Moist Tube (Mineral Sun Defense Moisturizer Broad Spectrum Sunscreen SPF 30)

Active Ingredients

Titanium Dioxide................4.31%

Zinc Oxide .......................19.27%

PURPOSE

Sunscreen

Uses

• helps prevent sunburn.

• if used as directed with other sun protection measures (see Directions) decreases the risk of skin cancer and early skin aging cause by the sun.

Warnings For external use only

Do not use on damaged or broken skin

When using this product keep out of eyes. Rinse with water to remove.

Stop use and ask a doctor if rash occurs.

Keep out of reach of children.

If swallowed, get medical help or contact a Poison Control Center right away.

Directions

• Apply liberally 15 minutes before sun exposure

• Reapply every 2 hours

• Use a water resistant sunscreen if swimming or sweating

• Children under 6 months of age: Ask a doctor

• Sun Protection Measures Spending time in the sun increases your risk of skin cancer and early skin aging. To decrease this risk, regularly use a sunscreen with a Broad Spectrum SPF value of 15 or higher and other sun protection measures including:

• limit time in the sun, especially from 10 a.m.- 2 p.m.

• wear long sleeved shirts, pants, hats and sunglasses

Other information • Protect the product in this container from excessive heat and direct sun

Inactive ingredients

Ethyl Macadamiate, Caprylic/Capric Triglyceride, Saccharomyces Ferment, Coco-Caprylate/Caprate, Behenyl Behenate, Sorbitol/ Sebacic Acid Copolymer Behenate, Polyhydroxystearic Acid, Octyldodecyl Erucate, Euphorbia Cerifera (Candelilla) Wax, Fragrance/Parfum, Lauroyl Lysine, Iron Oxides, Stearic Acid, Alumina, Glyceryl Caprylate, Butyrospermum Parkii (Shea) Butter, Persea Gratissima (Avocado) Oil , Argania Spinosa Kernel Oil, Tocopheryl Acetate, Polyglyceryl-6 Polyricinoleate, Dilinoleic Acid/Butanediol Copolymer, Tocopherol, Glyceryl Undecylenate, Malic Acid, Castor Oil/IPDI Copolymer, Glycerin, Lycium Barbarum Fruit Extract , Punica Granatum Extract, Vitis Vinifera (Grape) Seed Extract, Aspalathus Linearis Leaf Extract , Leuconostoc/Radish Root Ferment Filtrate, Camellia Sinensis Leaf Extract, Limonene, Linalool, Citral.

Questions or comments? Call toll free 1-866-586-3522